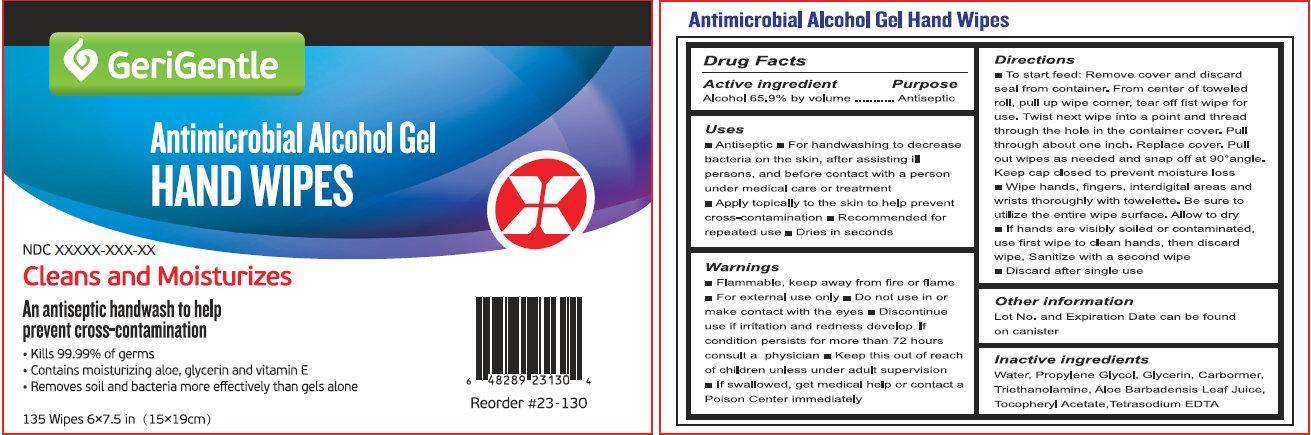 DRUG LABEL: Antimicrobial Alcohol Hand wipes
NDC: 69558-001 | Form: LIQUID
Manufacturer: GERI GENTILE CORP
Category: otc | Type: HUMAN OTC DRUG LABEL
Date: 20171227

ACTIVE INGREDIENTS: ALCOHOL 65.9 g/100 g
INACTIVE INGREDIENTS: WATER; PROPYLENE GLYCOL; GLYCERIN; TROLAMINE; ALOE VERA LEAF; .ALPHA.-TOCOPHEROL ACETATE; EDETATE SODIUM

GeriGentle Antimicrobial Alcohol Gel Hand wipes

Active ingredient

Alcohol 65.9% by volume

Purpose

Antiseptic

Uses

- Antiseptic.
- For hand washing to decrease bacteria on the skin; after assisting ill persons; and before contact with a person under medical care or treatment.
- Apply topically to the skin to help prevent cross-contamination
- Recommended for repeated use.
- Dries in seconds.

Warnings

- Flammable, keep away from fire or flame
- For external use only

• Do not use

in or contact the eyes

• Discontinue use

if irritation and redness develop，If condition persists for more than 72 hours consult a physician

• Keep this out of reach of children

unless under adult supervision • If swallowed, get medical help or contact a Poison Center immediately.

Directions

- To start feed: Remove cover and discard seal from container, From center of toweled roll , pull up wipe corner; tear off fist wipe for use. Twist next wipe into a point and thread through the hole in the container cover.Pull through about one inch. Replace cover,Pull out wipes as needed and snap off at 90°angle. Keep cap closed to prevent moisture loss.
- Wipe hands, fingers, interdigital areas and wrists thoroughly with towelette. Be sure to utilize the entire wipe surface. Allow to dry.
- If hands are visibly soiled or contaminated, use first wipe to clean hands, then discard wipe, Sanitize with a second wipe.
- Discard after single use.

Other information

Lot No.and Expiration Date can be found on canister.

Inactive ingredients

Water, Propylene Glycol, Glycerin, Carbormer, Triethanolamine, Aloe Barbadensis Leaf Juice, Tocopheryl Acetate, Tetrasodium EDTA

Package Label

GeriGental

Antimicrobial Alcohol Gel

HAND WIPES

Cleans and Moisturizes

An antiseptic handwash to help

prevent cross-contamination

- Kills 99.99% of germs
- Contains moisturizing aloe, glycerin and vitamin E
- Removes soil and bacteria more effectively than gels alone

135 Wipes 6x7.5 in (15x19cm)